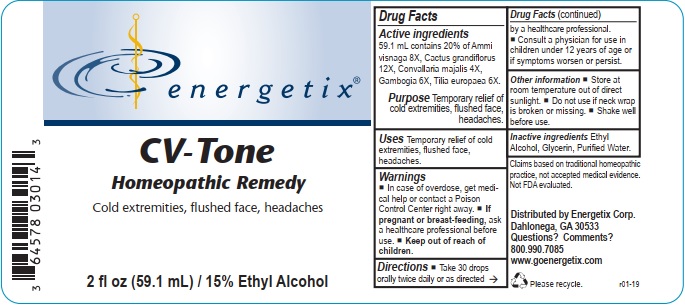 DRUG LABEL: CV-Tone
NDC: 64578-0113 | Form: LIQUID
Manufacturer: Energetix Corp
Category: homeopathic | Type: HUMAN OTC DRUG LABEL
Date: 20191217

ACTIVE INGREDIENTS: AMMI VISNAGA FRUIT 8 [hp_X]/1 mL; SELENICEREUS GRANDIFLORUS STEM 12 [hp_X]/1 mL; CONVALLARIA MAJALIS 4 [hp_X]/1 mL; GAMBOGE 6 [hp_X]/1 mL; TILIA X EUROPAEA FLOWER 6 [hp_X]/1 mL
INACTIVE INGREDIENTS: WATER; GLYCERIN; ALCOHOL

Drug Facts:

ACTIVE INGREDIENT

Active ingredients59.1 mL contains 20% of Ammi visnaga 8X, Cactus grandiflorus 12X, Convallaria majalis 4X, Gambogia 6X, Tilia europaea 6X.

Claims based on traditional homeopathic practice, not accepted medical evidence. Not FDA Evaluated.

INDICATIONS AND USAGE

Uses Temporary relief of cold extremities, flushed face, headaches.

Keep out of reach of children. In case of overdose, get medical help or contact a Poison Control Center right away.

If pregnant or breast feeding, ask a health professional before use.

Keep out of reach of children.

DOSAGE AND ADMINISTRATION

Take 30 drops orally twice daily or as directed by a healthcare professional.
Consult a physician for use in children under 12 years of age or if symptoms worsen or persist.

OTHER SAFETY INFORMATION

- Store at room temperature out of direct sunlight.
- Do not use if neck wrap is broken or missing.
- Shake well before use.

Inactive ingredients Ethyl Alcohol, Glycerin, Purified Water.

QUESTIONS

Distributed by Energetix Corp.
Dahlonega, GA 30533

Questions? Comments?

800.990.7085
www.goenergetix.com

PACKAGE LABEL

energetix
CV-Tone
Homeopathic Remedy
Cold extremities, flushed face, headaches
2 fl oz (59.1 mL) / 15% Ethyl Alcohol

PURPOSE

Purpose Temporary relief of cold extremities, flushed face, headaches.